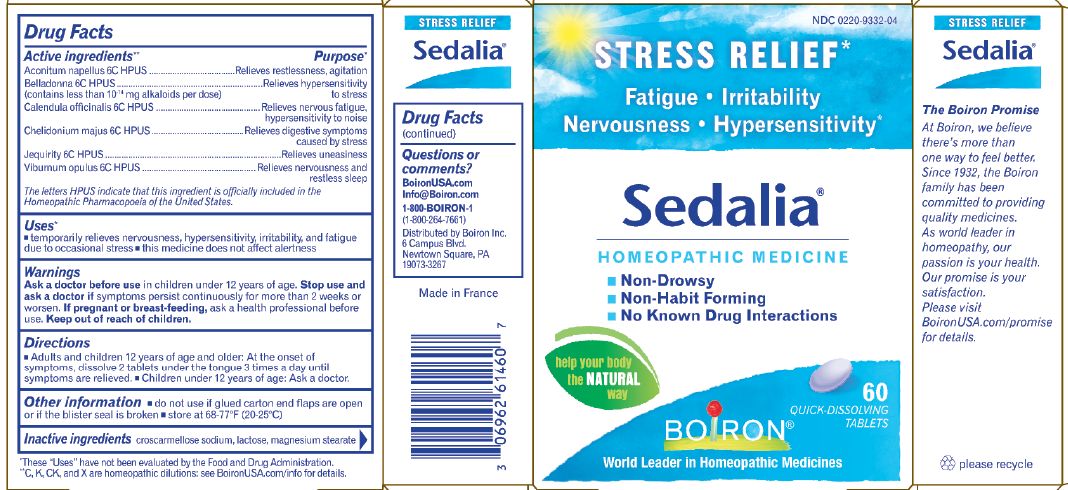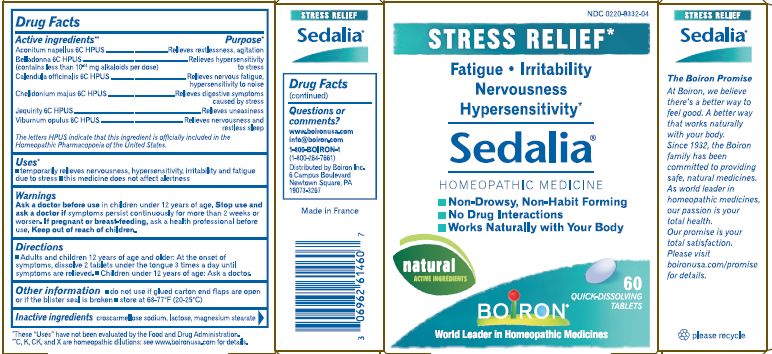 DRUG LABEL: Sedalia
NDC: 0220-9332 | Form: TABLET
Manufacturer: Laboratoires Boiron
Category: homeopathic | Type: HUMAN OTC DRUG LABEL
Date: 20180502

ACTIVE INGREDIENTS: ACONITUM NAPELLUS 6 [hp_C]/1 1; BELLADONNA LEAF 6 [hp_C]/1 1; CALENDULA OFFICINALIS FLOWERING TOP 6 [hp_C]/1 1; CHELIDONIUM MAJUS 6 [hp_C]/1 1; ABRUS PRECATORIUS SEED 6 [hp_C]/1 1; VIBURNUM OPULUS BARK 6 [hp_C]/1 1
INACTIVE INGREDIENTS: CROSCARMELLOSE SODIUM; LACTOSE; MAGNESIUM STEARATE

Sedalia

ACTIVE INGREDIENT

Aconitum napellus 6C, Belladona 6C, Calendula officinalis 6C, Chelidonium majus 6C, Jequirity 6C, Viburnum opulus 6C

PURPOSE

Aconitum napellus 6C Relieves restlessness, agitation
Belladona 6C Relieves hypersensitivity to stress
Calendula officinalis 6C Relieves nervous fatigue, hypersensitivity to noise
Chelidonium majus 6C Relieves digestive symptoms caused by stress
Jequirity 6C Relieves uneasiness
Viburnum opulus 6C Relieves nervousness and restless sleep

INDICATIONS AND USAGE

For temporary relief of nervousness, hypersensitivity and irritability due to stress.

Stop use and ask a doctor if symptoms persist continuously for more than 2 weeks or worsen.

Ask a doctor before use in children younger than 12 years of age.

WHEN USING

If pregnant or breast-feeding, ask a health professional before use.

Keep out of reach of children

DESCRIPTION

Directions: (adults and children 12 years of age and older): Allow 3 tablets to dissolve in the mouth 3 times a day.

STORAGE AND HANDLING

Store at 68-77o F (20-25o C)

Non habit forming, no drug interactions

INACTIVE INGREDIENT

Croscarmellose sodium, lactose, magnesium stearate.

Questions, Comments
www.boironusa.com
info@boironusa.com
1-800-BOIRON-1
(1-800-264-7661)
Boiron Information Center
6 campus Bouelvard
Newtown Square, PA
19073-3267

HOW SUPPLIED

60 tablets

DOSAGE AND ADMINISTRATION

Adult and children 12 years of age and older: dissolve 2 tablets in the mouth 3 times a day.